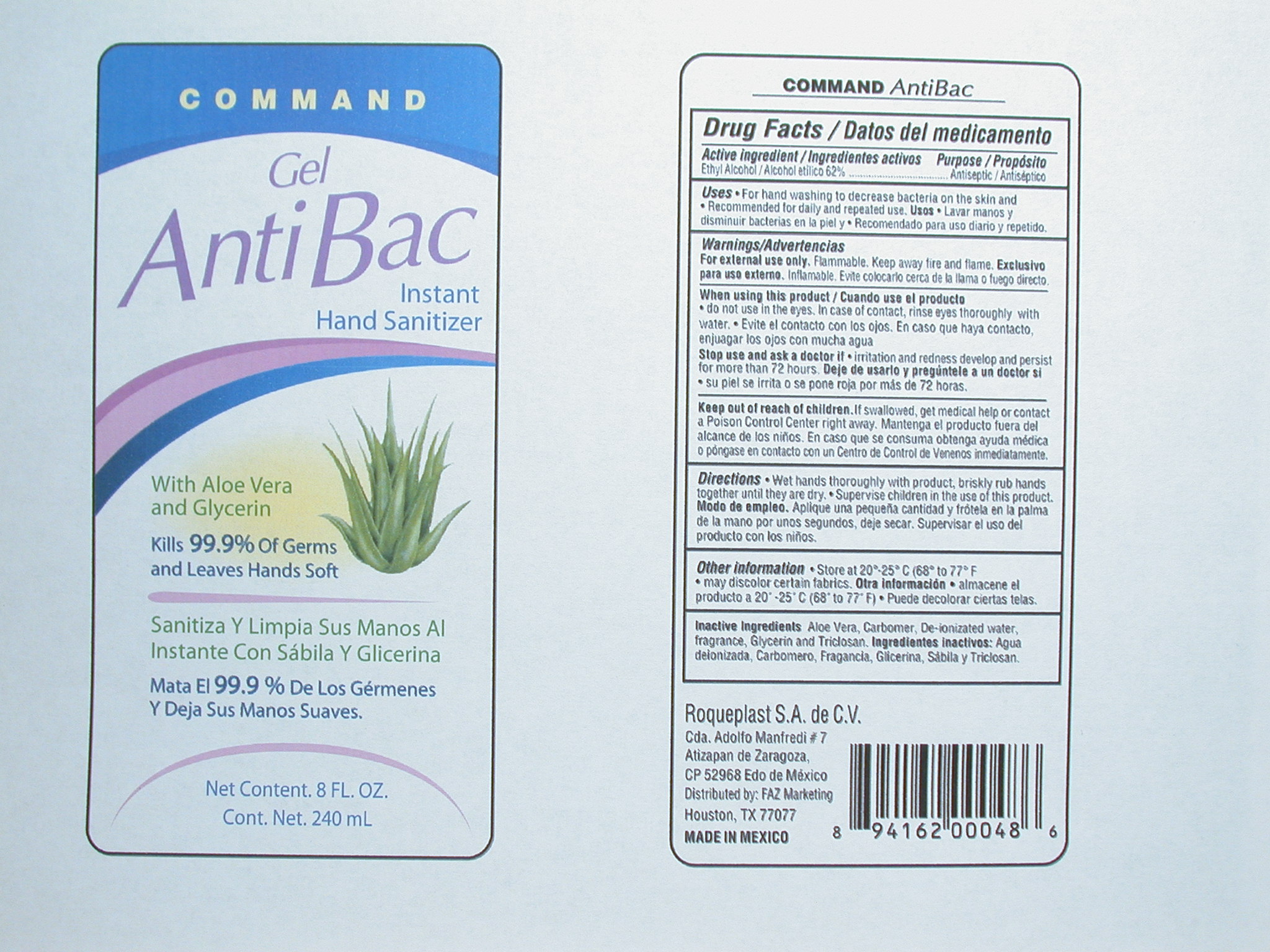 DRUG LABEL: Command AntiBac Instant Hand Sanitizer
NDC: 50061-001 | Form: LIQUID
Manufacturer: FAZ Marketing
Category: otc | Type: HUMAN OTC DRUG LABEL
Date: 20091210

ACTIVE INGREDIENTS: ALCOHOL 62 mL/100 mL
INACTIVE INGREDIENTS: ALOE VERA LEAF; WATER; GLYCERIN; TRICLOSAN

Drug Facts/Datos del medicamento

Active Ingredient/Ingredientes activos

Ethyl Alcohol/Alcohol etilico 62%

Purpose/Proposito

Antiseptic/Antiseptico

Uses

- For hand washing to decrease bacteria on the skin and
- Recommended for repeated use. Usos
- Lavar manos y disminuir bacterias en la piel y
- Recomendado par uso diario y repetido

Warnings/Advertencias

For external use only. Flammable. Keep away from fire and flame. Exclusivo para uso externo. Inflamable. Evite colocarlo cerca de la llama o fuego directo.

When using this product/Cuando use el producto

- do not use in the eyes. In case of contact, rinse eyes thoroughly with water.
- Evite el contacto con los ojos. En caso que haya contacto, enjuagar los ojos con mucha agua

Stop use and ask a doctor if

- irritation and redness develop an persist for more than 72 hours. Deje de usarlo y preguntele a un doctor si
- su piel se irrita o se pone roja por mas de 72 horas

Keep out of reach of children

If swallowed, get medical help or contact a Poison Control Center right away. Mantenga el producto fuera del alcance de los ninos. En caso que se consuma obtenga ayuda medica o pongase en contacto con un Centro de Control de Venenos inmediatamente.

Directions

- Wet hands thoroughly with product, briskly rub hands together until dry.
- Supervise children in the use of this product. Modo de empleo. Aplique una pequena cantidad y frotela en la palma de la mano por unos segundos, deje secar. Supervisar el uso del producto con los ninos

Other Information

- Store at 20-25C (68 to 77F)
- may discolor certain fabrics. Otra informacion
- almacene el producto 20-25C (68 to 77F)
- Puede decolorar ciertas telas

INACTIVE INGREDIENT

Inactive Ingredients Aloe Vera, Carbomer, Deionizated water, Fragrance, Glycerin and Triclosan. Ingredientes inactivos Agua deionizada, Carbomero, Fragancia, Glicerina, Sabila y Triclosan

Package Label